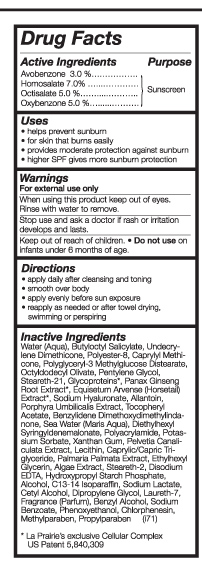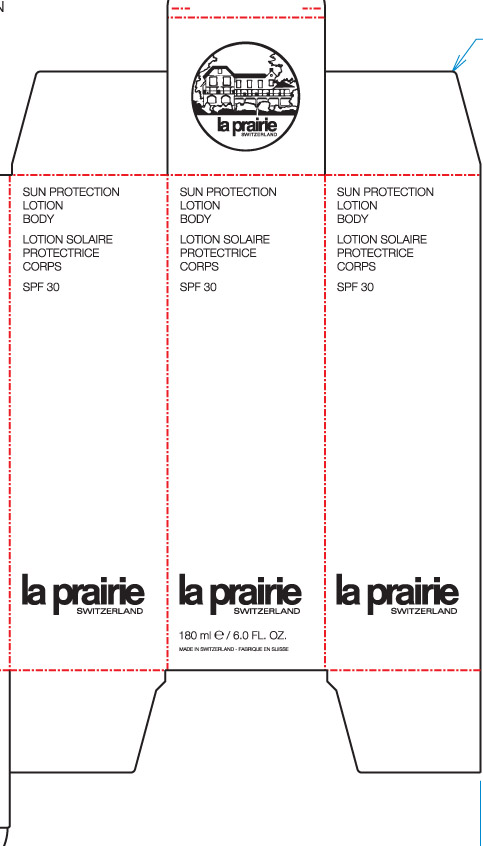 DRUG LABEL: Sun protection body 
NDC: 59614-511 | Form: LOTION
Manufacturer: Juvena Produits de Beaute GMBH
Category: otc | Type: HUMAN OTC DRUG LABEL
Date: 20110214

ACTIVE INGREDIENTS: AVOBENZONE 3 mL/100 mL; HOMOSALATE 7 mL/100 mL; OCTISALATE 5 mL/100 mL; OXYBENZONE 5 mL/100 mL
INACTIVE INGREDIENTS: BUTYLOCTYL SALICYLATE; HYALURONATE SODIUM; ALLANTOIN; MEDIUM-CHAIN TRIGLYCERIDES; EDETATE DISODIUM; C13-14 ISOPARAFFIN; CETYL ALCOHOL; DIPROPYLENE GLYCOL; LAURETH-7; METHYLPARABEN

Sun Protection Lotion Body SPF 30

Active ingredients Purpose

Avobenzone 3.0% sunscreen

Homosalate 7.0% sunscreen

Octisalate 5.0 % sunscreen

oxybenzone 5.0 % sunscreen

Keep out of reach of children
Do not use on infants under 6 months of age.

Stop use and ask a doctor if rash or irritation develops and lasts.

when using this product keep out of eyes. Rinse with water to remove.

DOSAGE AND ADMINISTRATION

- Apply daily after cleansing and toning

-smooth over body

-apply evenly before sun exposure

-reapply as needed or after towel drying, swimming or perspiring

INACTIVE INGREDIENT

Water (Aqua), Butyloctyl Salicaylate, Undecrylene Dimethicon, Polyester-8, Caprylyl Methicone, Polyglyceryl-3 Methylglucose Distearate, Octyldodecyl Olivate, Pentylene Glycol, Steareth-21, Glycoproteins, Panax Ginseng Root Extract, Equisetum Arvense (Horsetail) Extract, Sodium Hyaluronate, Allantoin, Porphyras Umbilicalis Extract, Tocopheryl Acetate, Benzylidene Dimethoxydimethylindanone, Sea Water (Maris Aqua) Diethylhexy Syringyldenemalonate, Polyacrylamide, Potassium Sorbate, Xanthan Gum , Pelvetia Canaliculate Extract, Lecithin, Caprylic/ Capric Triglyceride, Palmmaria Palmate Extract, Ethylhexyl Glycerin, Algae Extract, Steareth-2, Disodium EDTA, Hydroxypropyl Starch Phosphate, Alcohol. C13-14 Isoparaffin, Sodium Lactate, Cetyl Alcohol, Dipropylene Glycol, Laureth-7, Fragrance (Parfum), Benzyl Alcohol, Sodium Benzoate, Phenoxyethanol, Chlorphenesin, Methylparaben, Propylparaben

PACKAGE LABEL

Sun Protection lotion body SPF 30

180mL/ 6.0 FL.OZ